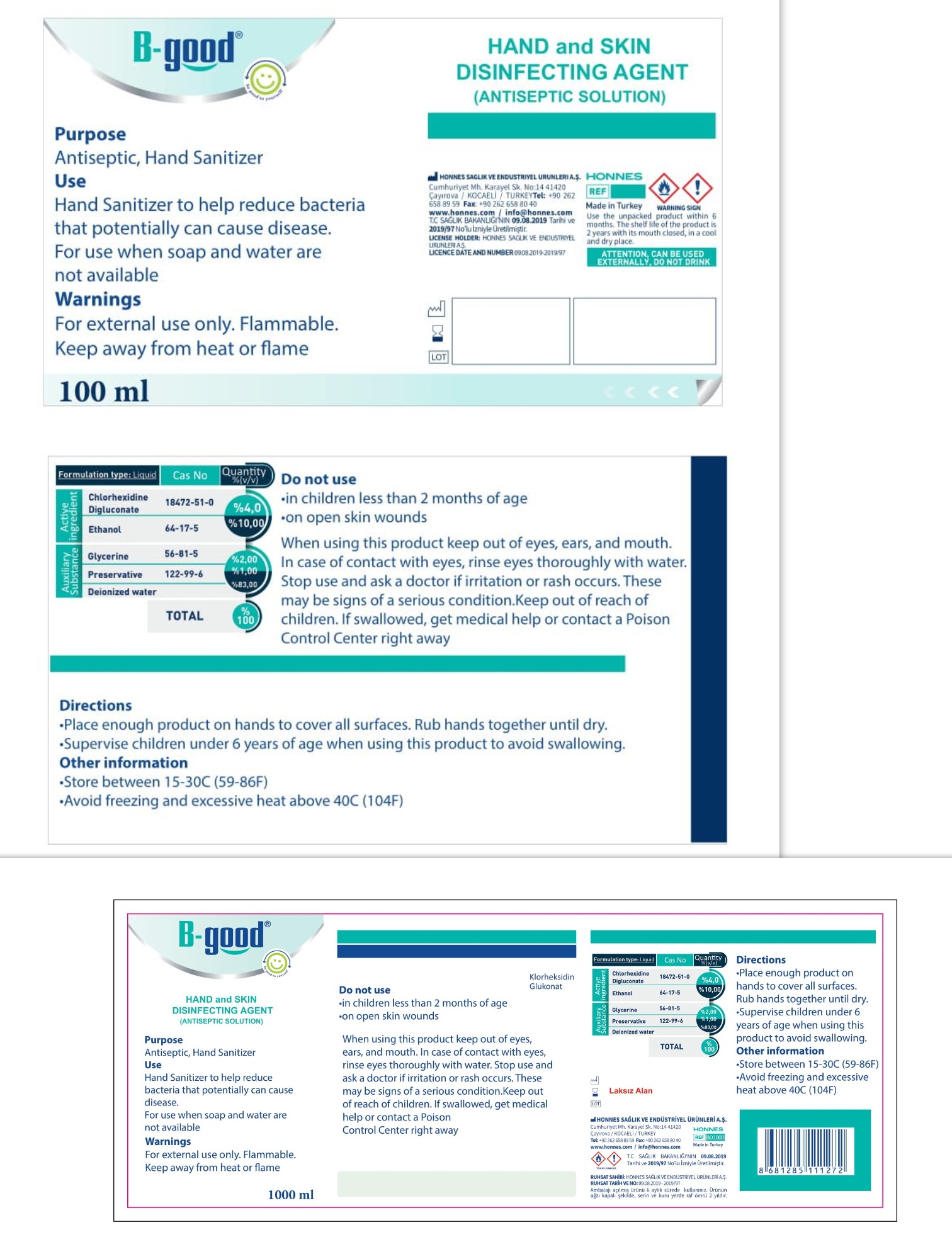 DRUG LABEL: B-GOOD HAND AND SKIN DISINFECTING AGENT
NDC: 79129-003 | Form: SOLUTION
Manufacturer: HONNES SAGLIK VE ENDUSTRIYEL URUNLERI ANONIM SIRKETI
Category: otc | Type: HUMAN OTC DRUG LABEL
Date: 20200703

ACTIVE INGREDIENTS: CHLORHEXIDINE GLUCONATE 4 mg/100 mL; ALCOHOL 10 mL/100 mL
INACTIVE INGREDIENTS: PHENOXYETHANOL; GLYCERIN; WATER

Solution

DESCRIPTION

B-GOOD HAND AND SKIN DISINFECTING AGENT (ANTISEPTIC SOLUTION)

Active Ingredient(s)

Clorhexidine Digluconate 4%, Ethanol 10%

Purpose

Antiseptic, Hand Sanitizer

Use

Hand Sanitizer to help reduce bacteria that potentially can cause disease. For use when soap and water are not available.

Warnings

For external use only. Flammable. Keep away from heat or flame

Do not use

- in children less than 2 months of age
- on open skin wounds

When using this product keep out of eyes, ears, and mouth. In case of contact with eyes, rinse eyes thoroughly with water.

Stop use and ask a doctor if irritation or rash occurs. These may be signs of a serious condition.

Keep out of reach of children. If swallowed, get medical help or contact a Poison Control Center right away.

Directions

- Place enough product on hands to cover all surfaces. Rub hands together until dry.
- Supervise children under 6 years of age when using this product to avoid swallowing.

Other information

- Store between 15-30C (59-86F)
- Avoid freezing and excessive heat above 40C (104F)

Inactive ingredients

Glycerine, Preservative, Deionized water

Package Label - Principal Display Panel

Producer

HONNES SAGLIK VE ENDUSTRIYEL URUNLERI A.S.

Cumhuriyet Mh. Karayel Sk. No:14 41420

Cayirova/KOCAELI/TURKEY

Tel.: +90 262 658 89 59

Fax: +90 262 658 80 40

www.honnes.com / info@honnes.com

T.C. SAGLIK BAKANLIGI'NIN 09.08.2019 Tarihi ve 2019/97 No'lu Izniyle Uretilmistir.

LICENSE HOLDER: HONNES SAGLIK VE ENDUSTRIYEL URUNLERI A.S.

LICENCE DATE AND NUMBER 09.08.2019-2019/97

ATTENTION, CAN BE USED EXTERNALLY, DO NOT DRINK

Use the unpacked product within 6 months. The shelf life of the product is 2 years with its mouth closed, in a cool and dry place.